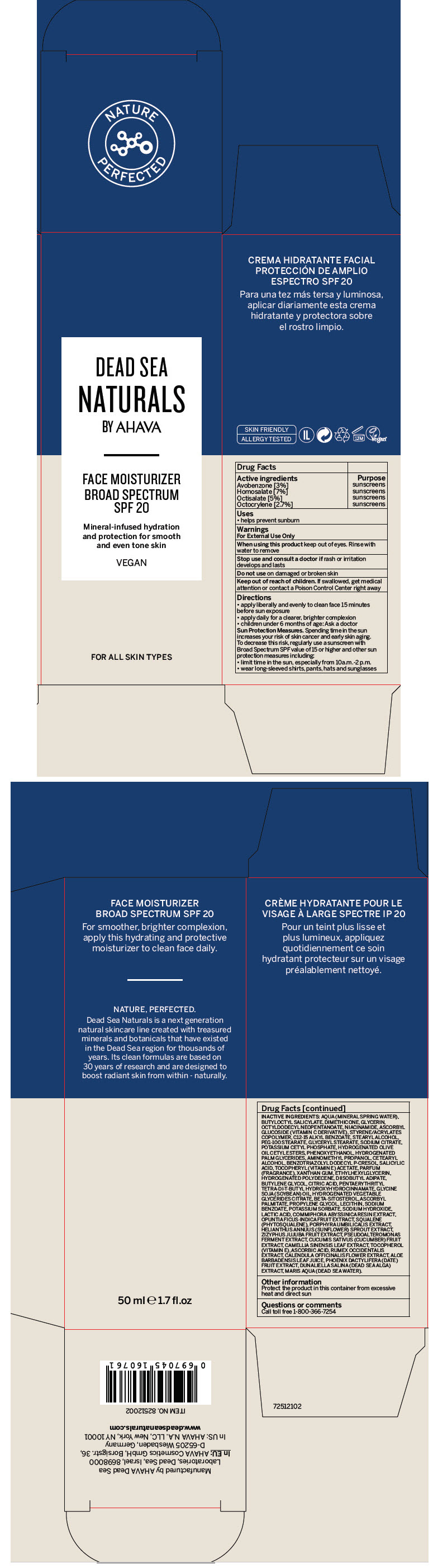 DRUG LABEL: Dead Sea Natural 
NDC: 60289-291 | Form: CREAM
Manufacturer: AHAVA Dead Sea Laboratories Ltd
Category: otc | Type: HUMAN OTC DRUG LABEL
Date: 20231108

ACTIVE INGREDIENTS: Avobenzone 30 mg/1 mL; Homosalate 70 mg/1 mL; Octisalate 50 mg/1 mL; Octocrylene 27 mg/1 mL
INACTIVE INGREDIENTS: WATER; BUTYLOCTYL SALICYLATE; DIMETHICONE; GLYCERIN; OCTYLDODECYL NEOPENTANOATE; NIACINAMIDE; ASCORBYL GLUCOSIDE; STYRENE/ACRYLAMIDE COPOLYMER (500000 MW); ALKYL (C12-15) BENZOATE; STEARYL ALCOHOL; PEG-100 STEARATE; GLYCERYL MONOSTEARATE; SODIUM CITRATE, UNSPECIFIED FORM; POTASSIUM CETYL PHOSPHATE; HYDROGENATED OLIVE OIL CETYL ESTERS; PHENOXYETHANOL; HYDROGENATED PALM GLYCERIDES; AMINOMETHYLPROPANOL; CETOSTEARYL ALCOHOL; BENZOTRIAZOLYL DODECYL P-CRESOL; SALICYLIC ACID; .ALPHA.-TOCOPHEROL; XANTHAN GUM; ETHYLHEXYLGLYCERIN; DIISOBUTYL ADIPATE; BUTYLENE GLYCOL; CITRIC ACID MONOHYDRATE; PENTAERYTHRITOL TETRAKIS(3-(3,5-DI-TERT-BUTYL-4-HYDROXYPHENYL)PROPIONATE); SOYBEAN OIL; .BETA.-SITOSTEROL; ASCORBYL PALMITATE; PROPYLENE GLYCOL; SODIUM BENZOATE; POTASSIUM SORBATE; SODIUM HYDROXIDE; LACTIC ACID, UNSPECIFIED FORM; COMMIPHORA MADAGASCARIENSIS RESIN; PRICKLY PEAR FRUIT; PORPHYRA UMBILICALIS; HELIANTHUS ANNUUS SPROUT; JUJUBE FRUIT; CUCUMBER; GREEN TEA LEAF; ASCORBIC ACID; CALENDULA OFFICINALIS FLOWER; ALOE VERA LEAF; DATE

Dead Sea Natural
Face Moisturizer Broad Spectrum SPF 20

Drug Facts

ACTIVE INGREDIENT

Active ingredients | Purpose
Avobenzone [3%] | sunscreens
Homosalate [7%] | sunscreens
Octisalate [5%] | sunscreens
Octocrylene [2.7%] | sunscreens

Uses

- helps prevent sunburn

Warnings

For External Use Only

When using this product keep out of eyes. Rinse with water to remove

Stop use and consult a doctor if rash or irritation develops and lasts

Do not use on damaged or broken skin

Keep out of reach of children. If swallowed, get medical attention or contact a Poison Control Center right away

Directions

- apply liberally and evenly to clean face 15 minutes before sun exposure
- apply daily for a clearer, brighter complexion
- children under 6 months of age: Ask a doctor

Sun Protection Measures. Spending time in the sun increases your risk of skin cancer and early skin aging. To decrease this risk, regularly use a sunscreen with Broad Spectrum SPF value of 15 or higher and other sun protection measures including:

- limit time in the sun, especially from 10a.m.-2 p.m.
- wear long-sleeved shirts, pants, hats and sunglasses

INACTIVE INGREDIENTS

AQUA (MINERAL SPRING WATER), BUTYLOCTYL SALICYLATE, DIMETHICONE, GLYCERIN, OCTYLDODECYL NEOPENTANOATE, NIACINAMIDE, ASCORBYL GLUCOSIDE (VITAMIN C DERIVATIVE), STYRENE/ACRYLATES COPOLYMER, C12-15 ALKYL BENZOATE, STEARYL ALCOHOL, PEG-100 STEARATE, GLYCERYL STEARATE, SODIUM CITRATE, POTASSIUM CETYL PHOSPHATE, HYDROGENATED OLIVE OIL CETYL ESTERS, PHENOXYETHANOL, HYDROGENATED PALM GLYCERIDES, AMINOMETHYL PROPANOL, CETEARYL ALCOHOL, BENZOTRIAZOLYL DODECYL P-CRESOL, SALICYLIC ACID, TOCOPHERYL (VITAMIN E) ACETATE, PARFUM (FRAGRANCE), XANTHAN GUM, ETHYLHEXYLGLYCERIN, HYDROGENATED POLYDECENE, DIISOBUTYL ADIPATE, BUTYLENE GLYCOL, CITRIC ACID, PENTAERYTHRITYL TETRA-DI-T-BUTYL HYDROXYHYDROCINNAMATE, GLYCINE SOJA (SOYBEAN) OIL, HYDROGENATED VEGETABLE GLYCERIDES CITRATE, BETA-SITOSTEROL, ASCORBYL PALMITATE, PROPYLENE GLYCOL, LECITHIN, SODIUM BENZOATE, POTASSIUM SORBATE, SODIUM HYDROXIDE, LACTIC ACID, COMMIPHORA ABYSSINICA RESIN EXTRACT, OPUNTIA FICUS-INDICA FRUIT EXTRACT, SQUALENE (PHYTOSQUALENE), PORPHYRA UMBILICALIS EXTRACT, HELIANTHUS ANNUUS (SUNFLOWER) SPROUT EXTRACT, ZIZYPHUS JUJUBA FRUIT EXTRACT, PSEUDOALTEROMONAS FERMENT EXTRACT, CUCUMIS SATIVUS (CUCUMBER) FRUIT EXTRACT, CAMELLIA SINENSIS LEAF EXTRACT, TOCOPHEROL (VITAMIN E), ASCORBIC ACID, RUMEX OCCIDENTALIS EXTRACT, CALENDULA OFFICINALIS FLOWER EXTRACT, ALOE BARBADENSIS LEAF JUICE, PHOENIX DACTYLIFERA (DATE) FRUIT EXTRACT, DUNALIELLA SALINA (DEAD SEA ALGA) EXTRACT, MARIS AQUA (DEAD SEA WATER).

Other information

Protect the product in this container from excessive heat and direct sun

Questions or comments

Call toll free 1-800-366-7254

Manufactured by AHAVA Dead Sea
Laboratories, Dead Sea, Israel, 8698000

PRINCIPAL DISPLAY PANEL - 50 ml Tube Carton

DEAD SEA
NATURALS

BY AHVANA

FACE MOISTURIZER
BROAD SPECTRUM
SPF 20

Mineral-infused hydration
and protection for smooth
and even tone skin

VEGAN

FOR ALL SKIN TYPES